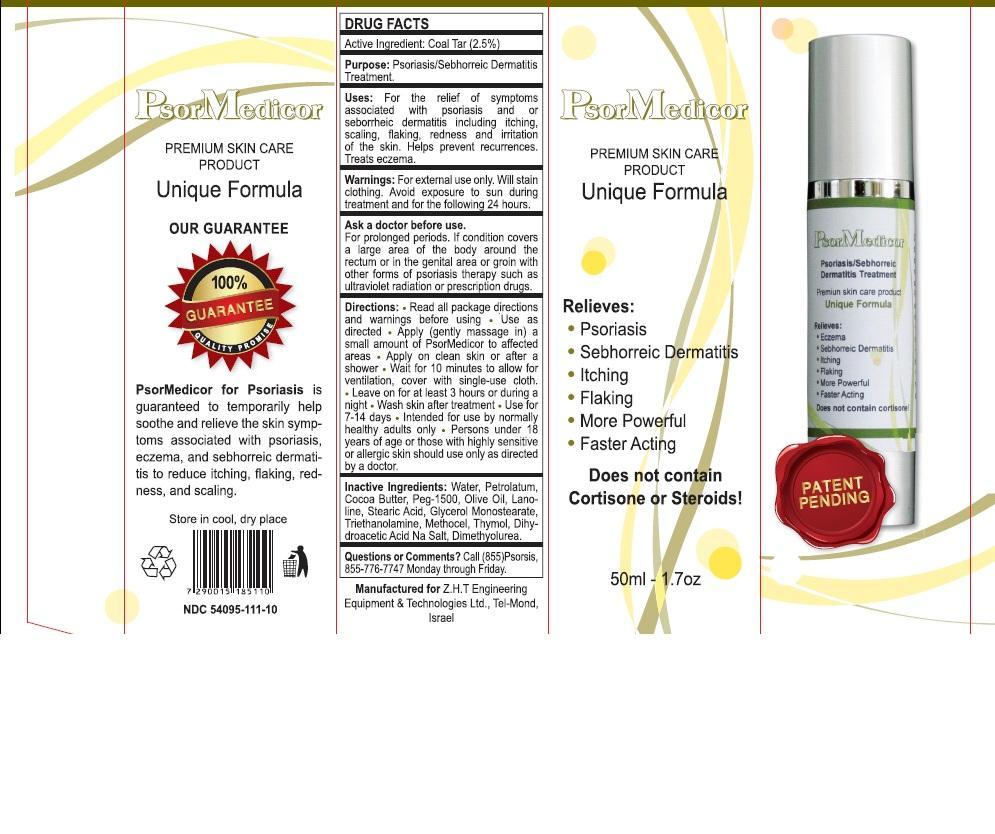 DRUG LABEL: PsorMedicor
NDC: 54095-111 | Form: OINTMENT
Manufacturer: Z.H.T. ENGINEERING EQUIPMENT AND TECHNOLOGIES LTD
Category: otc | Type: HUMAN OTC DRUG LABEL
Date: 20131111

ACTIVE INGREDIENTS: COAL TAR 2.5 g/100 g
INACTIVE INGREDIENTS: WATER; PETROLATUM; COCOA BUTTER; POLYETHYLENE GLYCOL 1500; OLIVE OIL; LANOLIN; STEARIC ACID; GLYCERYL MONOSTEARATE; TROLAMINE; THYMOL; 1,3-DIMETHYLUREA

DRUG FACTS

Active Ingredient:

Coal Tar (2.5%)

Purpose:

Psoriasis/Sebhorreic Dermatitis Treatment

Uses:

For the relief of symptoms associated with psoriasis and or seborrheic dermatitis including itching, scaling, flaking, redness and irritation of the skin. Helps prevent recurrences. Treats eczema.

Warnings:

For external use only. Will stain clothing. Avoid exposure to sun during treatment and for the following 24 hours.

Ask a doctor before use.

For prolonged periods. If condition covers a large area of the body around the rectum or in the genital area or groin with other forms of psoriasis therapy such as ultraviolet radiation or prescription.

Directions:

- Read all package directions and warnings before using.
- Use as directed.
- Apply (gently massage in) a small amount of PsorMedicor to affected areas.
- Apply on clean skin or after a shower.
- Wait for 10 minutes to allow for ventilation, cover with single-use cloth.
- Leave on for at least 3 hours or during a night.
- Wash skin after treatment.
- Use for 7-14 days.
- Intended for use by normally healthy adults only.
- Persons under 18 years of age or those with highly sensitive or allergic skin should use only as directed by a doctor.

Questions or Comments?

Call (865) Psorsis, 855-776-7747 Monday through Friday.

Inactive Ingredients:

Water, Petrolatum, Cocoa Butter, PEG - 1500, Olive Oil, Lanolin, Stearic Acid, Glycerol Monostearate, Triethanolamine, Methocel, Thymol, Dihydroacetic acid Na Salt, Dimethylurea.

Principal Display Panel

PsorMedicor

PREMIUM SKIN CARE

PRODUCT

Unique Formula

Relieves:

- Psoriasis
- Sebhorreic Dermatitis
- Itching
- Flaking
- More Powerful
- Faster Acting

Does not contain Cortisone or Steroids!

PATENT PENDING

50 ml - 1.7 oz